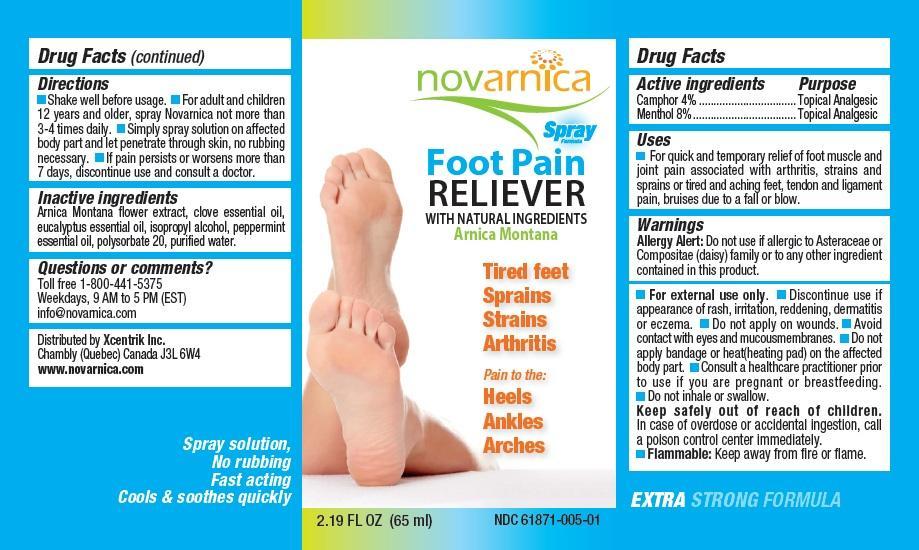 DRUG LABEL: Novarnica Foot Pain Reliever
NDC: 61871-005 | Form: SPRAY
Manufacturer: Xcentrik Inc.
Category: otc | Type: HUMAN OTC DRUG LABEL
Date: 20221219

ACTIVE INGREDIENTS: CAMPHOR (NATURAL) 4 g/100 mL; MENTHOL 8 g/100 mL
INACTIVE INGREDIENTS: ARNICA MONTANA FLOWER; CLOVE OIL; EUCALYPTUS OIL; ISOPROPYL ALCOHOL; PEPPERMINT OIL; POLYSORBATE 20; WATER

Drug Facts

Active ingredients

Camphor 4%
Menthol 8%

Purpose

Topical Analgesic

Uses

For quick and temporary relief of foot muscle and joint pain associated with arthritis, strains and sprains or tired and aching feet, tendon and ligament pain, bruises due to a fall or blow.

Warnings

Allergy Alert: Do not use if allergic to Asteraceae or Compositae (daisy) family or to any other ingredient contained in this product.

- For external use only.
- Discontinue use if appearance of rash, irritation, reddening, dermatitis or eczema.
- Do not apply on wounds.
- Avoid contact with eyes and mucous membranes.
- Do not apply bandage or heat (heating pad) on the affected body part.
- Consult a healthcare practitioner prior to use if you are pregnant or breastfeeding.
- Do not inhale or swallow.

KEEP OUT OF REACH OF CHILDREN

- Keep safely out of reach of children. In case of overdose or accidental ingestion, call a poison control center immediately.
- Flammable: Keep away from fire or flame.

Directions

- Shake well before usage.
- For adult and children 12 years and older, spray Novarnica on affected area 3-4 times daily.
- Let penetrate through skin, no rubbing necessary.
- If pain persists or worsens more than 7 days, discontinue use and consult a doctor.

Inactive ingredients

Arnica Montana flower extract, clove essential oil, eucalyptus essential oil, isopropyl alcohol, peppermint essential oil, polysorbate 20, purified water.

Questions or comments?

Toll free 1-800-441-5375
Weekdays, 9 AM to 5 PM (EST)
info@novarnica.com

Distributed by Xcentrik Inc.
7902 Samuel Hatt
Chambly (Quebec) Canada J3L 6W4
www.novarnica.com

Principal Display Panel

novarnica

Spray Formula

Foot Pain RELIEVER
WITH NATURAL INGREDIENTS
Arnica Montana

Tired feet
Sprains
Strains
Arthritis

Pain to the:
Heels
Ankles
Arches

2.19 FL OZ (65 ml) NDC 61871-005-01